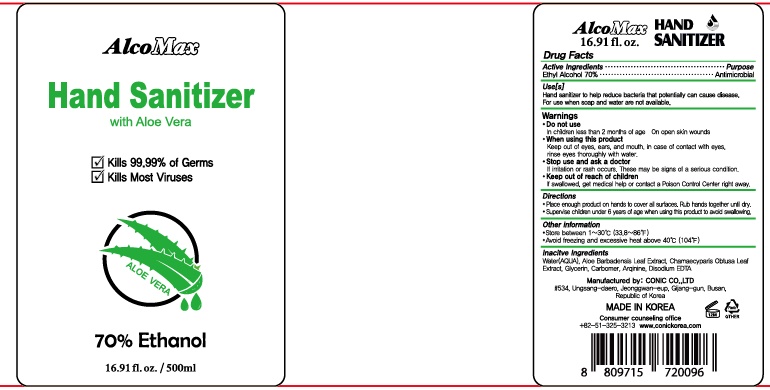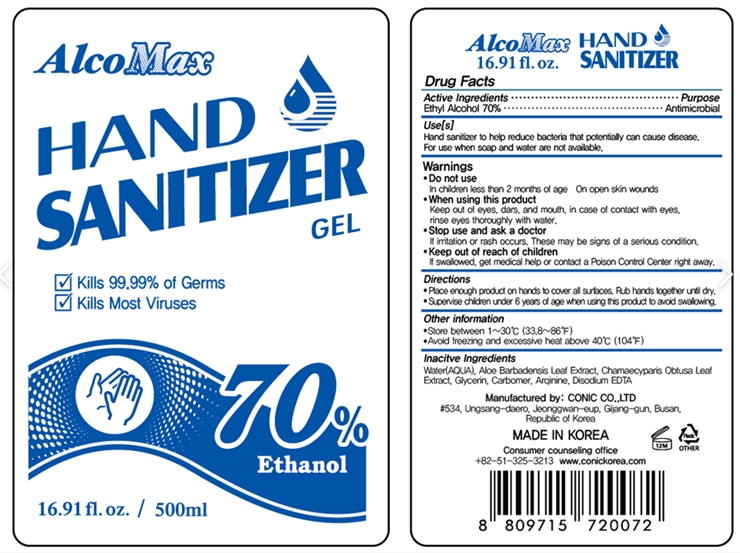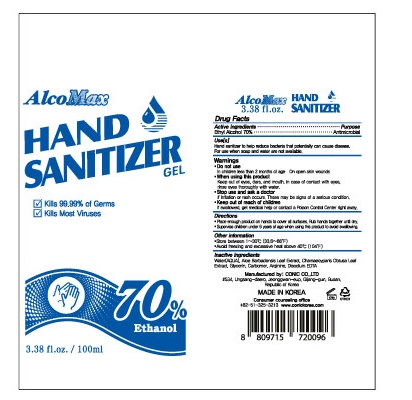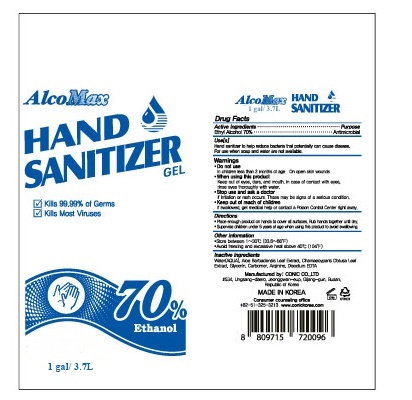 DRUG LABEL: AlcoMax
NDC: 75700-301 | Form: GEL
Manufacturer: CONIC CO., LTD.
Category: otc | Type: HUMAN OTC DRUG LABEL
Date: 20201125

ACTIVE INGREDIENTS: ALCOHOL 70 mL/100 mL
INACTIVE INGREDIENTS: EDETATE DISODIUM ANHYDROUS 2.5 mL/100 mL; GLYCERIN 3 mL/100 mL; CHAMAECYPARIS OBTUSA LEAF 2 mL/100 mL; CARBOMER HOMOPOLYMER, UNSPECIFIED TYPE 3.5 mL/100 mL; ALOE VERA LEAF 2 mL/100 mL; ARGININE 4 mL/100 mL; WATER 13 mL/100 mL

Active Ingredient

ALCHOL 70%

PURPOSE

ANTIMICROBIAL

Inactive Ingredient

Water, Aloe Barbadensis leaf, chamaecyparis Obtusa leaf, Glycerin, Carbomer, Arqinine, DISODIUM EDTA

Direction

Place enough product on hands to cover all surfaces.Rub hands together until dry.

Supervise children under 6 years of age when using this product to avoid swallowing.

Do not use

In children less than 2 months of age .

On open skin wounds

When using this product

Keep out of eyes, ears, and mouth in case of contact with eyes, rinse eyes thoroughly whit water.

Warnings

for external sue only. Flammable. keep away from heat or flame

Keep out of reach of children.

If swallowed get medical help or contact a Poison Control center right away.

Stop use and ask a doctor.

if irritationor rash occurs. These may be signs of a serious contion.

Use

Hand sanitizer to help reduce bacteria that potentially can cause disease.

For use when soap and water are not avaliable.

Other information

Store between 33.8~86'F

Avoid freezing and excessive heat

Pakage Label

3.7L 75700-301-04

100ml 75700-301-03

500ml 75700-301-02 (new)

500ml 75700-301-01